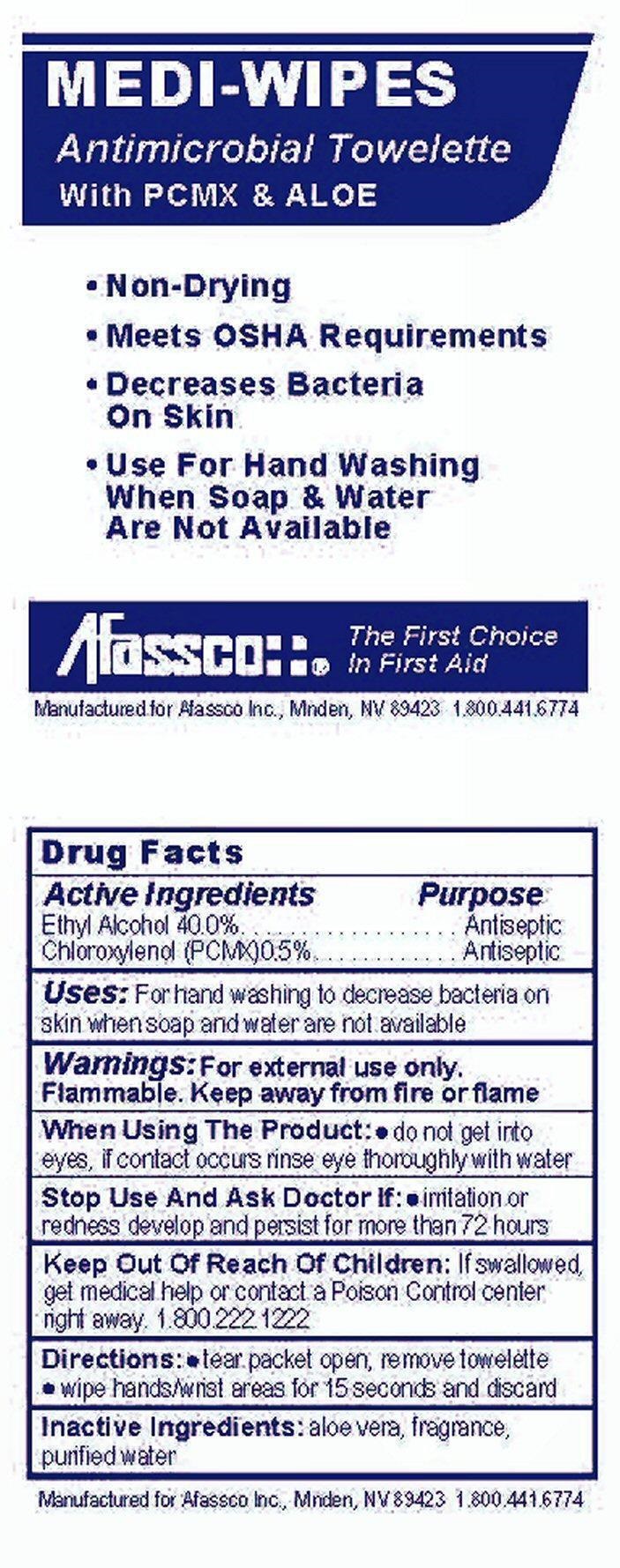 DRUG LABEL: MEDI-WIPES
NDC: 51532-5104 | Form: SWAB
Manufacturer: Afassco Inc
Category: otc | Type: HUMAN OTC DRUG LABEL
Date: 20191223

ACTIVE INGREDIENTS: ALCOHOL 0.6 g/1.5 g; CHLOROXYLENOL 7.5 g/1.5 g
INACTIVE INGREDIENTS: ALOE VERA LEAF; WATER

Drug Facts Active Ingredients

Ethyl Alcohol 40.0%

Chloroxylenol (PCMX) 0.5%

Purpose

Antiseptic

Uses:

For hand washing to decrease bacteria on skin when soap and water are not available.

Warnings:

For external use only.

Flammable. Keep away from fire or flame

Directions:

- tear packet open, remove towelette
- wipe hands/wrist areas for 15 seconds and discard

When Using The Product:

- do not get into eyes. If contact occurs rinse eye thoroughly with water

Stop Use And Ask Doctor If:

- irritation or redness develop and persist for more than 72 hours

Inactive Ingredients:

aloe vera, fragrance, purified water

Keep Out Of Reach Of Children

If swallowed, get medical help or contact a Poison Control center right away. 1-800-222-1222

Product Label Medi-Wipes

MEDI-WIPES

Antimicrobial Towelette With PCMX and ALOE

Afassco::® The First Choice In First Aid

Manufactured for Afassco Inc, Minden, NV 89423 1.800.441.6774

Non-Drying
Meets OSHA Requirements
Decreases Bacteria On Skin
Use For Hand Washing When Soap And Water Are Not Available

res